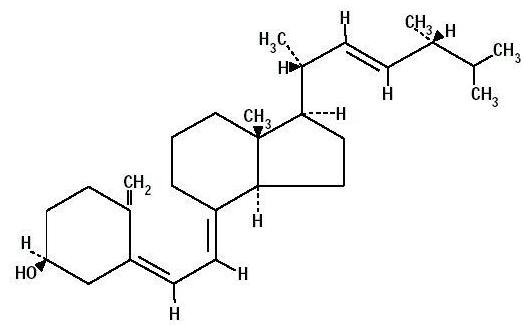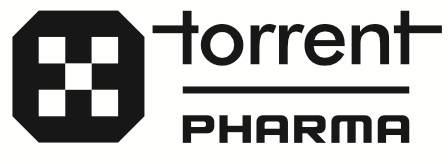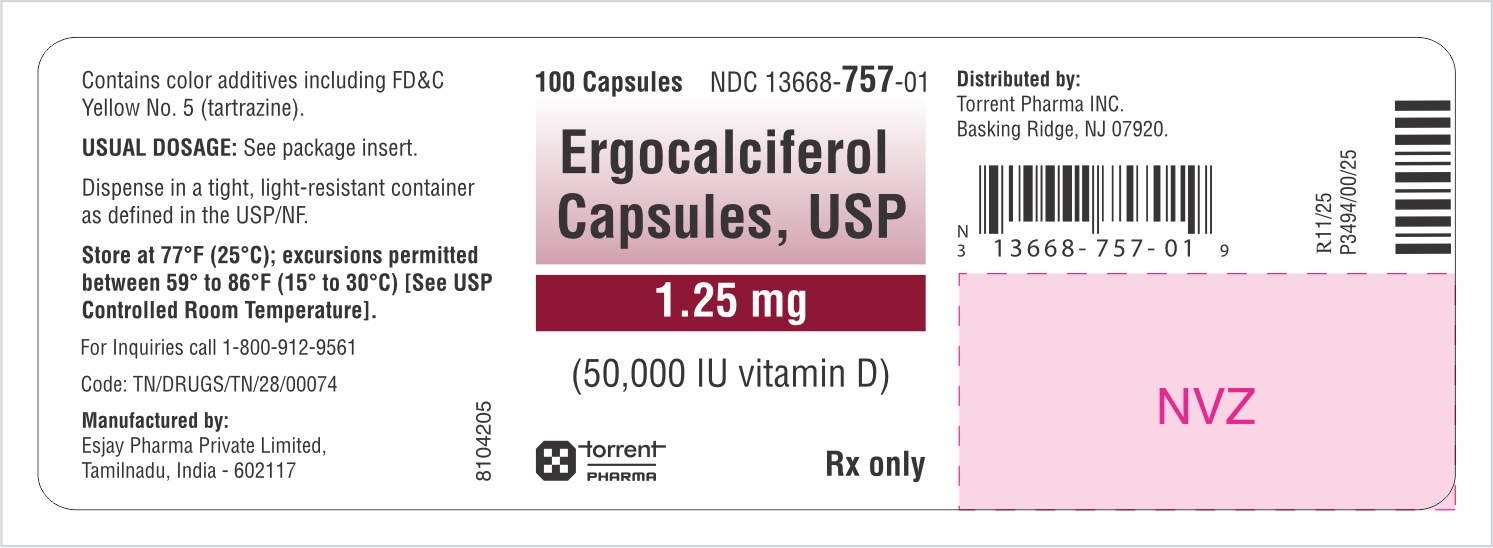 DRUG LABEL: ERGOCALCIFEROL
NDC: 13668-757 | Form: CAPSULE
Manufacturer: Torrent Pharmaceuticals Limited
Category: prescription | Type: Human Prescription Drug Label
Date: 20260122

ACTIVE INGREDIENTS: ERGOCALCIFEROL 1.25 mg/1 1
INACTIVE INGREDIENTS: FD&C BLUE NO. 1; FD&C YELLOW NO. 5; GELATIN; GLYCERIN; SOYBEAN OIL; BUTYLATED HYDROXYANISOLE; WATER

Ergocalciferol capsules, USP
50,000 IU Capsules

DESCRIPTION

Ergocalciferol capsules, USP, is a synthetic calcium regulator for oral administration.

Ergocalciferol is a white, colorless crystal, insoluble in water, soluble in organic solvents, and slightly soluble in vegetable oils. It is affected by air and by light. Ergosterol or provitamin D2 is found in plants and yeast and has no antirachitic activity.

There are more than 10 substances belonging to a group of steroid compounds, classified as having vitamin D or antirachitic activity.

One USP unit of vitamin D2 is equivalent to one International Unit (IU), and 1 mcg of vitamin D2 is equal to 40 IU.

Each capsule contains 1.25 mg (50,000 International Units vitamin D) of ergocalciferol, USP, in an edible vegetable oil.

Ergocalciferol, also called vitamin D2, is 9, 10-secoergosta-5,7,10 (19), 22-tetraen-3-ol, (3ß,5Z,7E,22E)-; (C28H44O) with a molecular weight of 396.65, and has the following structural formula:

Inactive Ingredients: Butylated Hydroxylanisole, FD&C Blue #1, FD&C Yellow #5, Gelatin, Glycerin, Purified Water, Soybean Oil.

CLINICAL PHARMACOLOGY

The in vivo synthesis of the major biologically active metabolites of vitamin D occurs in two steps. The first hydroxylation of ergocalciferol takes place in the liver (to 25-hydroxyvitamin D) and the second in the kidneys (to 1, 25-dihydroxyvitamin D). Vitamin D metabolites promote the active absorption of calcium and phosphorus by the small intestine, thus elevating serum calcium and phosphate levels sufficiently to permit bone mineralization.
Vitamin D metabolites also mobilize calcium and phosphate from bone and probably increase the reabsorption of calcium and perhaps also of phosphate by the renal tubules.

There is a time lag of 10 to 24 hours between the administration of vitamin D and the initiation of its action in the body due to the necessity of synthesis of the active metabolites in the liver and kidneys. Parathyroid hormone is responsible for the regulation of this metabolism in the kidneys.

INDICATIONS AND USAGE

Ergocalciferol is indicated for use in the treatment of hypoparathyroidism, refractory rickets, also known as vitamin D resistant rickets, and familial hypophosphatemia.

CONTRAINDICATIONS

Ergocalciferol is contraindicated in patients with hypercalcemia, malabsorption syndrome, abnormal sensitivity to the toxic effects of vitamin D, and hypervitaminosis D.

WARNINGS

Hypersensitivity to vitamin D may be one etiologic factor in infants with idiopathic hypercalcemia. In these cases vitamin D must be strictly restricted.

Keep out of the reach of children.

PRECAUTIONS

General

Vitamin D administration from fortified foods, dietary supplements, self-administered and prescription drug sources should be evaluated. Therapeutic dosage should be readjusted as soon as there is clinical improvement. Dosage levels must be individualized and great care exercised to prevent serious toxic effects. IN VITAMIN D RESISTANT RICKETS THE RANGE BETWEEN THERAPEUTIC AND TOXIC DOSES IS NARROW. When high therapeutic doses are used progress should be followed with frequent blood calcium determinations.

In the treatment of hypoparathyroidism, intravenous calcium, parathyroid hormone, and/or dihydrotachysterol may be required.

Maintenance of a normal serum phosphorus level by dietary phosphate restriction and/or administration of aluminum gels as intestinal phosphate binders in those patients with hyperphosphatemia as frequently seen in renal osteodystrophy is essential to prevent metastatic calcification.

Adequate dietary calcium is necessary for clinical response to vitamin D therapy.

This product contains FD&C Yellow No. 5 (tartrazine) which may cause allergic-type reactions (including bronchial asthma) in certain susceptible individuals. Although the overall incidence of FD&C Yellow No. 5 (tartrazine) sensitivity in the general population is low, it is frequently seen in patients who also have aspirin hypersensitivity.

Protect from light.

Drug Interactions

Mineral oil interferes with the absorption of fat-soluble vitamins, including vitamin D preparations.

Administration of thiazide diuretics to hypoparathyroid patients who are concurrently being treated with ergocalciferol may cause hypercalcemia.

Carcinogenesis, Mutagenesis, Impairment of Fertility

No long-term animal studies have been performed to evaluate the drug’s potential in these areas.

Pregnancy

Animal reproduction studies have shown fetal abnormalities in several species associated with hypervitaminosis D. These are similar to the supravalvular aortic stenosis syndrome described in infants by Black in England (1963). This syndrome was characterized by supravalvular aortic stenosis, elfin facies, and mental retardation. For the protection of the fetus, therefore, the use of vitamin D in excess of the recommended dietary allowance during normal pregnancy should be avoided unless, in the judgment of the physician, potential benefits in a specific, unique case outweigh the significant hazards involved. The safety in excess of 400 IU of vitamin D daily during pregnancy has not been established.

Nursing Mothers

Caution should be exercised when ergocalciferol is administered to a nursing woman. In a mother given large doses of vitamin D, 25-hydroxycholecalciferol appeared in the milk and caused hypercalcemia in her child. Monitoring of the infant’s serum calcium concentration is required in that case (Goldberg, 1972).

Pediatric Use

Pediatric doses must be individualized (see DOSAGE AND ADMINISTRATION).

Geriatric Use

Clinical studies of ergocalciferol did not include sufficient numbers of subjects aged 65 and over to determine whether they respond differently from younger subjects. Other reported clinical experience has not identified differences in responses between the elderly and younger patients. A few published reports have suggested that the absorption of orally administered vitamin D may be attenuated in elderly compared to younger individuals. In
general, dose selection for an elderly patient should be cautious, usually starting at the low end of the dosing range, reflecting the greater frequency of decreased hepatic, renal, or cardiac function, and of concomitant disease or other drug therapy.

ADVERSE REACTIONS

Hypervitaminosis D is characterized by effects on the following organ system:

Renal: Impairment of renal function with polyuria, nocturia, polydipsia, hypercalciuria, reversible azotemia, hypertension, nephrocalcinosis, generalized vascular calcification, or irreversible renal insufficiency which may result in death.

CNS: Mental retardation.

Soft Tissues: Widespread calcification of the soft tissues, including the heart, blood vessels, renal tubules, and lungs.

Skeletal: Bone demineralization (osteoporosis) in adults occurs concomitantly.

Decline in the average rate of linear growth and increased mineralization of bones in infants and children (dwarfism) vague aches, stiffness, and weakness.

Gastrointestinal: Nausea, anorexia, constipation.

Metabolic: Mild acidosis, anemia, weight loss.

To report SUSPECTED ADVERSE REACTIONS, contact Torrent Pharma Inc. at 1-800-912-9561 or FDA at 1-800-FDA-1088 or www.fda.gov/medwatch.

OVERDOSAGE

The effects of administered vitamin D can persist for two or more months after cessation of treatment.

Hypervitaminosis D is characterized by:

1. Hypercalcemia with anorexia, nausea, weakness, weight loss, vague aches and stiffness, constipation, mental retardation, anemia, and mild acidosis.

2. Impairment of renal function with polyuria, nocturia, polydipsia, hypercalciuria, reversible azotemia, hypertension, nephrocalcinosis, generalized vascular calcification, or irreversible renal insufficiency which may result in death.
3. Widespread calcification of the soft tissues, including the heart, blood vessels, renal tubules, and lungs. Bone demineralization (osteoporosis) in adults occurs concomitantly.
4. Decline in the average rate of linear growth and increased mineralization of bones in infants and children (dwarfism).

The treatment of hypervitaminosis D with hypercalcemia consists in immediate withdrawal of the vitamin, a low calcium diet, generous intake of fluids, along with symptomatic and supportive treatment. Hypercalcemic crisis with dehydration, stupor, coma, and azotemia requires more vigorous treatment. The first step should be hydration of the patient. Intravenous saline may quickly and significantly increase urinary calcium excretion.
A loop diuretic (furosemide or ethacrynic acid) may be given with the saline infusion to further increase renal calcium excretion. Other reported therapeutic measures include dialysis or the administration of citrates, sulfates, phosphates, corticosteroids, EDTA (ethylenediaminetetraacetic acid), and mithramycin via appropriate regimens. With appropriate therapy, recovery is the usual outcome when no permanent damage has occurred. Deaths via renal or cardiovascular failure have been reported.

The LD50 in animals is unknown. The toxic oral dose of ergocalciferol in the dog is 4 mg/kg.

DOSAGE AND ADMINISTRATION

THE RANGE BETWEEN THERAPEUTIC AND TOXIC DOSES IS NARROW.

Vitamin D Resistant Rickets: 12,000 to 500,000 IU units daily.

Hypoparathyroidism: 50,000 to 200,000 IU units daily concomitantly with calcium lactate 4 g, six times per day.

DOSAGE MUST BE INDIVIDUALIZED UNDER CLOSE MEDICAL SUPERVISION.

Calcium intake should be adequate. Blood calcium and phosphorus determinations must be made every 2 weeks or more frequently if necessary.

X-rays of the bones should be taken every month until condition is corrected and stabilized.

HOW SUPPLIED

Capsules of 1.25 mg (50,000 IU vitamin D) of ergocalciferol, USP are clear, forest green, oval, soft gelatin capsules laser printed with “E09” supplied in HDPE bottles:

Bottles of 100 - NDC 13668-757-01

Store at 77°F (25°C); excursions permitted between 59° to 86°F (15° to 30°C) [See USP Controlled Room Temperature].

Dispense in a tight, light-resistant container as defined in the USP/NF.

Rx Only

Manufactured by:
Esjay Pharma Private Limited,
Tamilnadu, India - 602117

Distributed by:
Torrent Pharma INC.
Basking Ridge, NJ 07920.

8104206

P3495/00/25

Rev. 11/2025

PACKAGE LABEL.PRINCIPAL DISPLAY PANEL

Container Label 100's counts